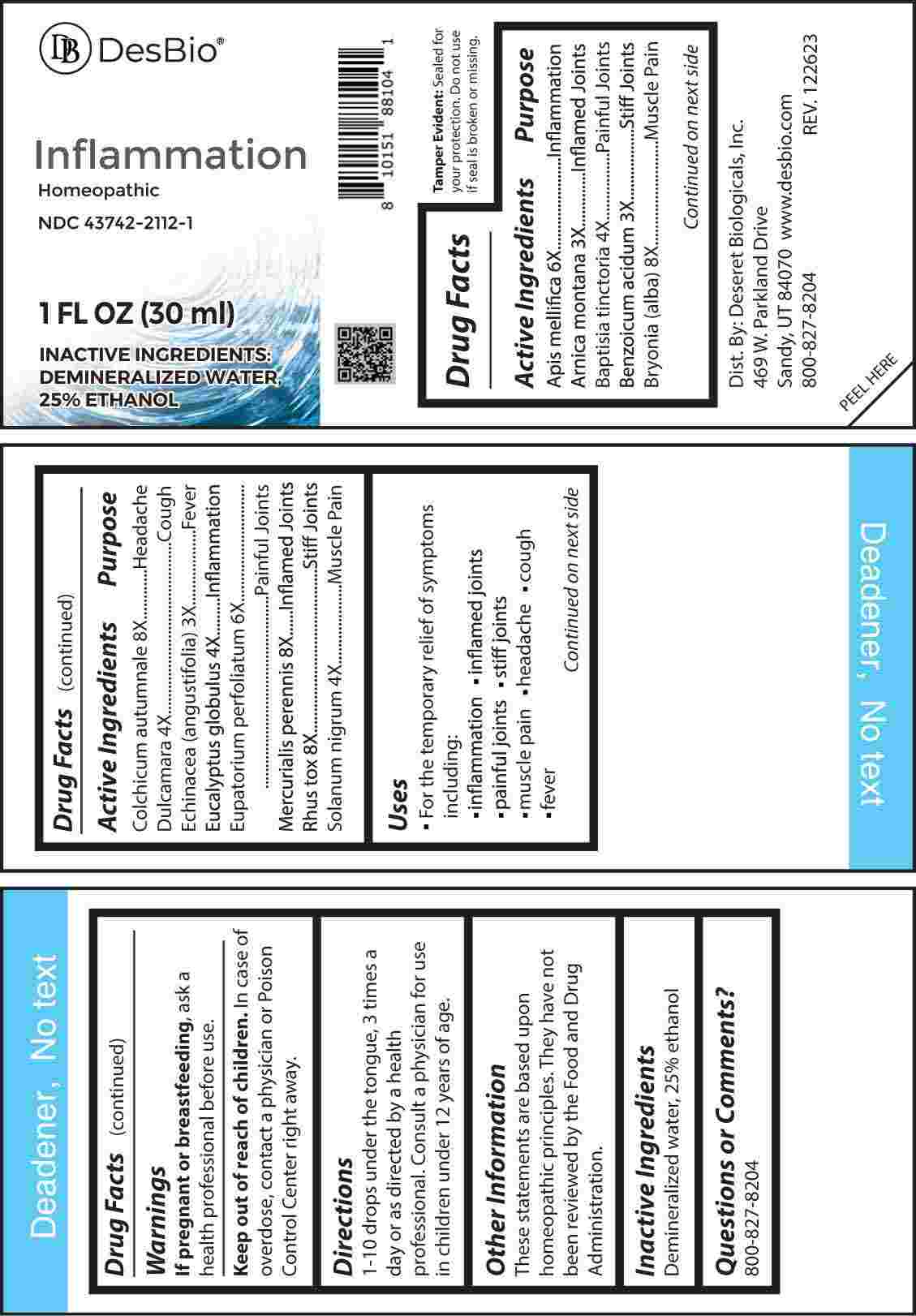 DRUG LABEL: Inflammation
NDC: 43742-2112 | Form: LIQUID
Manufacturer: Deseret Biologicals, Inc.
Category: homeopathic | Type: HUMAN OTC DRUG LABEL
Date: 20240408

ACTIVE INGREDIENTS: APIS MELLIFERA 6 [hp_X]/1 mL; ARNICA MONTANA WHOLE 3 [hp_X]/1 mL; BAPTISIA TINCTORIA ROOT 4 [hp_X]/1 mL; BENZOIC ACID 3 [hp_X]/1 mL; BRYONIA ALBA ROOT 8 [hp_X]/1 mL; COLCHICUM AUTUMNALE BULB 8 [hp_X]/1 mL; SOLANUM DULCAMARA TOP 4 [hp_X]/1 mL; ECHINACEA ANGUSTIFOLIA WHOLE 3 [hp_X]/1 mL; EUCALYPTUS GLOBULUS LEAF 4 [hp_X]/1 mL; EUPATORIUM PERFOLIATUM FLOWERING TOP 6 [hp_X]/1 mL; MERCURIALIS PERENNIS WHOLE 8 [hp_X]/1 mL; TOXICODENDRON PUBESCENS LEAF 8 [hp_X]/1 mL; SOLANUM NIGRUM WHOLE 4 [hp_X]/1 mL
INACTIVE INGREDIENTS: WATER; ALCOHOL

DRUG FACTS:

ACTIVE INGREDIENTS:

Apis Mellifica 6X, Arnica Montana 3X, Baptisia Tinctoria 4X, Benzoicum Acidum 3X, Bryonia (Alba) 8X, Colchicum Autumnale 8X, Dulcamara 4X, Echinacea (Angustifolia) 3X, Eucalyptus Globulus 4X, Eupatorium Perfoliatum 6X, Mercurialis Perennis 8X, Rhus Tox 8X, Solanum Nigrum 4X.

PURPOSE

Apis Mellifica - Inflammation, Arnica Montana – Inflamed Joints, Baptisia Tinctoria – Painful Joints, Benzoicum Acidum – Stiff Joints, Bryonia (Alba) – Muscle Pain, Colchicum Autumnale - Headache, Dulcamara - Cough, Echinacea (Angustifolia) - Fever, Eucalyptus Globulus - Inflammation, Eupatorium Perfoliatum – Painful Joints, Mercurialis Perennis – Inflamed Joints, Rhus Tox – Stiff Joints, Solanum Nigrum – Muscle Pain

USES:

• For the temporary relief of symptoms including:

• inflammation • inflamed joints • painful joints

• stiff joints • muscle pain • headache • cough • fever

These statements are based upon homeopathic principles. They have not been reviewed by the Food and Drug Administration.

WARNINGS:

If pregnant or breast-feeding, ask a health professional before use.

Keep out of reach of children. In case of overdose, contact a physician or Poison Control Center right away.

Tamper Evident: Sealed for your protection. Do not use if seal is broken or missing.

KEEP OUT OF REACH OF CHILDREN:

In case of overdose, contact a physician or Poison Control Center right away.

DIRECTIONS:

1-10 drops under the tongue, 3 times a day or as directed by a health professional. Consult a physician for use in children under 12 years of age.

INACTIVE INGREDIENTS:

Demineralized water, 25% ethanol

QUESTIONS:

Dist. By: Deseret Biologicals, Inc.

469 W. Parkland Drive

Sandy, UT 84070

www.desbio.com

800-827-8204

PACKAGE LABEL DISPLAY:

DesBio

Inflammation

Homeopathic

NDC 43742-2112-1

1 FL OZ (30 ml)